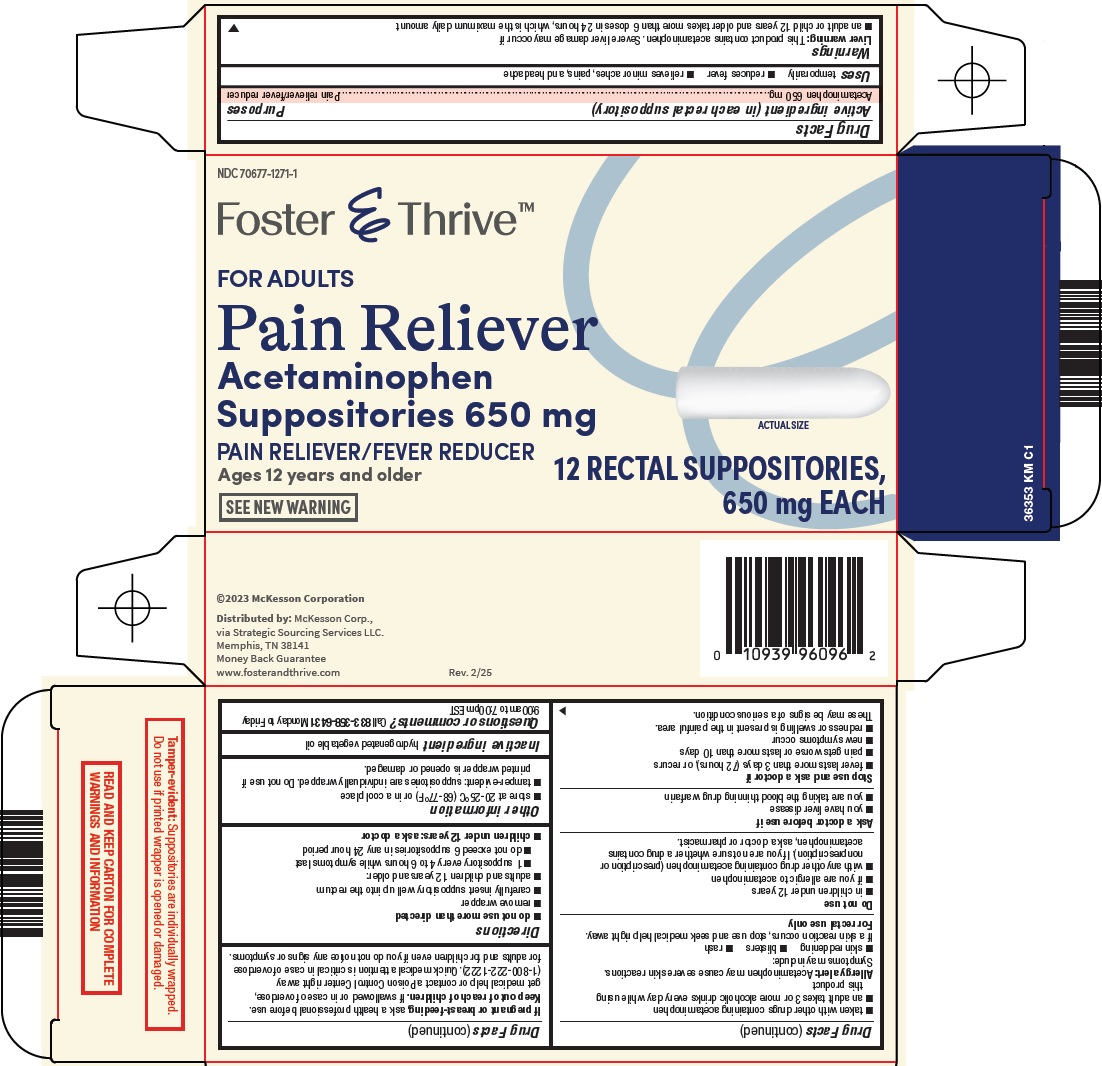 DRUG LABEL: foster and thrive pain reliever
NDC: 70677-1271 | Form: SUPPOSITORY
Manufacturer: Strategic Sourcing Services LLC
Category: otc | Type: HUMAN OTC DRUG LABEL
Date: 20250415

ACTIVE INGREDIENTS: ACETAMINOPHEN 650 mg/1 1
INACTIVE INGREDIENTS: COTTONSEED OIL

Mckesson Pain Reliever Drug Facts

Active ingredient (in each rectal suppository)

Acetaminophen 650 mg

Purposes

Pain reliever/fever reducer

Uses

temporarily

- reduces fever
- relieves minor aches, pains, and headache

Warnings

Liver warning:

This product contains acetaminophen. Severe liver damage may occur if

- an adult or child 12 years and older takes more than 6 doses in 24 hours, which is the maximum daily amount
- taken with other drugs containing acetaminophen
- an adult takes 3 or more alcoholic drinks every day while using this product

Allergy alert: Acetaminophen may cause severe skin reactions. Symptoms may include:

- skin reddening
- blisters
- rash

If a skin reaction occurs, stop use and seek medical help right away.

For rectal use only

Do not use

- in children under 12 years
- if you are allergic to acetaminophen
- with any other drug containing acetaminophen (prescription or nonprescription). If you are not sure whether a drug contains acetaminophen, ask a doctor or pharmacist.

Ask a doctor before use if

- you have liver disease
- you are taking the blood thinning drug warfarin

Stop use and ask a doctor if

- fever lasts more than 3 days (72 hours), or recurs
- pain gets worse or lasts more than 10 days
- new symptoms occur
- redness or swelling is present in the painful area.

These may be signs of a serious condition.

If pregnant or breast-feeding,

ask a health professional before use.

Keep out of reach of children.

If swallowed or in case of overdose, get medical help or contact a Poison Control Center right away (1-800-222-1222). Quick medical attention is critical in case of overdose for adults and for children even if you do not notice any signs or symptoms.

Directions

- do not use more than directed
- remove wrapper
- carefully insert suppository well up into the rectum
- adults and children 12 years and older:
- 1 suppository every 4 to 6 hours while symptoms last
- do not exceed 6 suppositories in any 24 hour period
- children under 12 years: ask a doctor

Other information

- store at 20-25°C (68-77°F) or in a cool place
- tamper-evident: suppositories are individually wrapped. Do not use if printed wrapper is opened or damaged.

Inactive ingredient

hydrogenated vegetable oil

Questions or comments?

Call 833-358-6431 Monday to Friday 9:00am to 7:00pm EST

Principal Display Panel

Foster & ThriveTM

FOR ADULTS

Pain Reliever

Acetaminophen Suppositories 650 mg

ACTUAL SIZE

PAIN RELIEVER/FEVER REDUCER

12 RECTAL SUPPOSITORIES, 650 mg EACH

Ages 12 years and older

SEE NEW WARNING